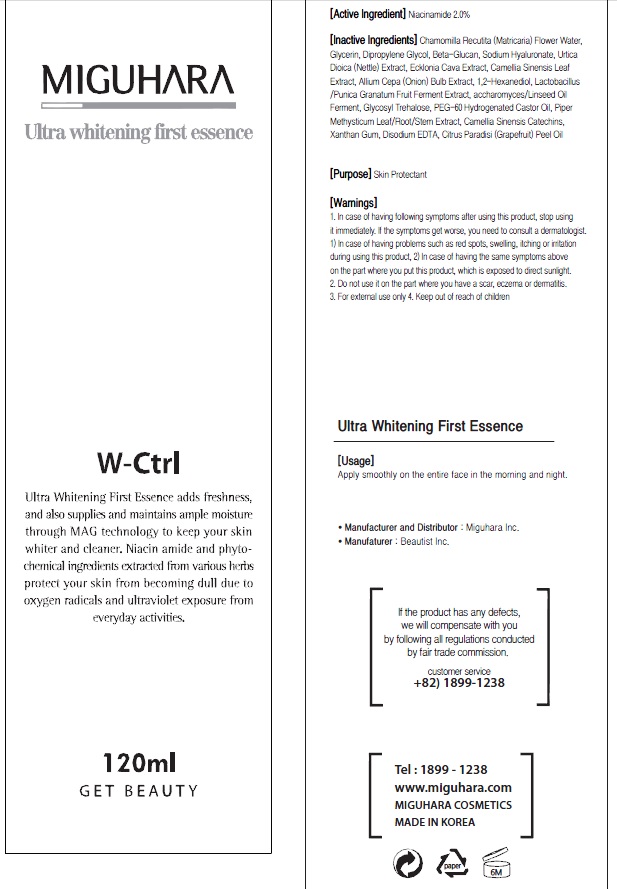 DRUG LABEL: Ultra Whitening First Essence
NDC: 70380-330 | Form: CREAM
Manufacturer: MIGUHARA
Category: otc | Type: HUMAN OTC DRUG LABEL
Date: 20160224

ACTIVE INGREDIENTS: Niacinamide 2.4 g/120 mL
INACTIVE INGREDIENTS: CHAMOMILE; Glycerin

ACTIVE INGREDIENT

Active Ingredient: Niacinamide 2.0%

INACTIVE INGREDIENT

Inactive Ingredients: Chamomilla Recutita (Matricaria) Flower Water, Glycerin, Dipropylene Glycol, Beta-Glucan, Sodium Hyaluronate, Urtica Dioica (Nettle) Extract, Ecklonia Cava Extract, Camellia Sinensis Leaf Extract, Allium Cepa (Onion) Bulb Extract, 1,2-Hexanediol, Lactobacillus/Punica Granatum Fruit Ferment Extract, accharomyces/Linseed Oil Ferment, Glycosyl Trehalose, PEG-60 Hydrogenated Castor Oil, Piper Methysticum Leaf/Root/Stem Extract, Camellia Sinensis Catechins, Xanthan Gum, Disodium EDTA, Citrus Paradisi (Grapefruit) Peel Oil

PURPOSE

Purpose: Skin Protectant

WARNINGS

1. In case of having following symptoms after using this product, stop using it immediately. If the symptoms get worse, you need to consult a dermatologist. 1) In case of having problems such as red spots, swelling, itching or irritation during using this product, 2) In case of having the same symptoms above on the part where you put this product, which is exposed to direct sunlight. 2. Do not use it on the part where you have a scar, eczema or dermatitis. 3. For external use only 4. Keep out of reach of children

KEEP OUT OF REACH OF CHILDREN

Usage

Usage: Apply smoothly on the entire face in the morning and night.

Usage

Usage: Apply smoothly on the entire face in the morning and night.